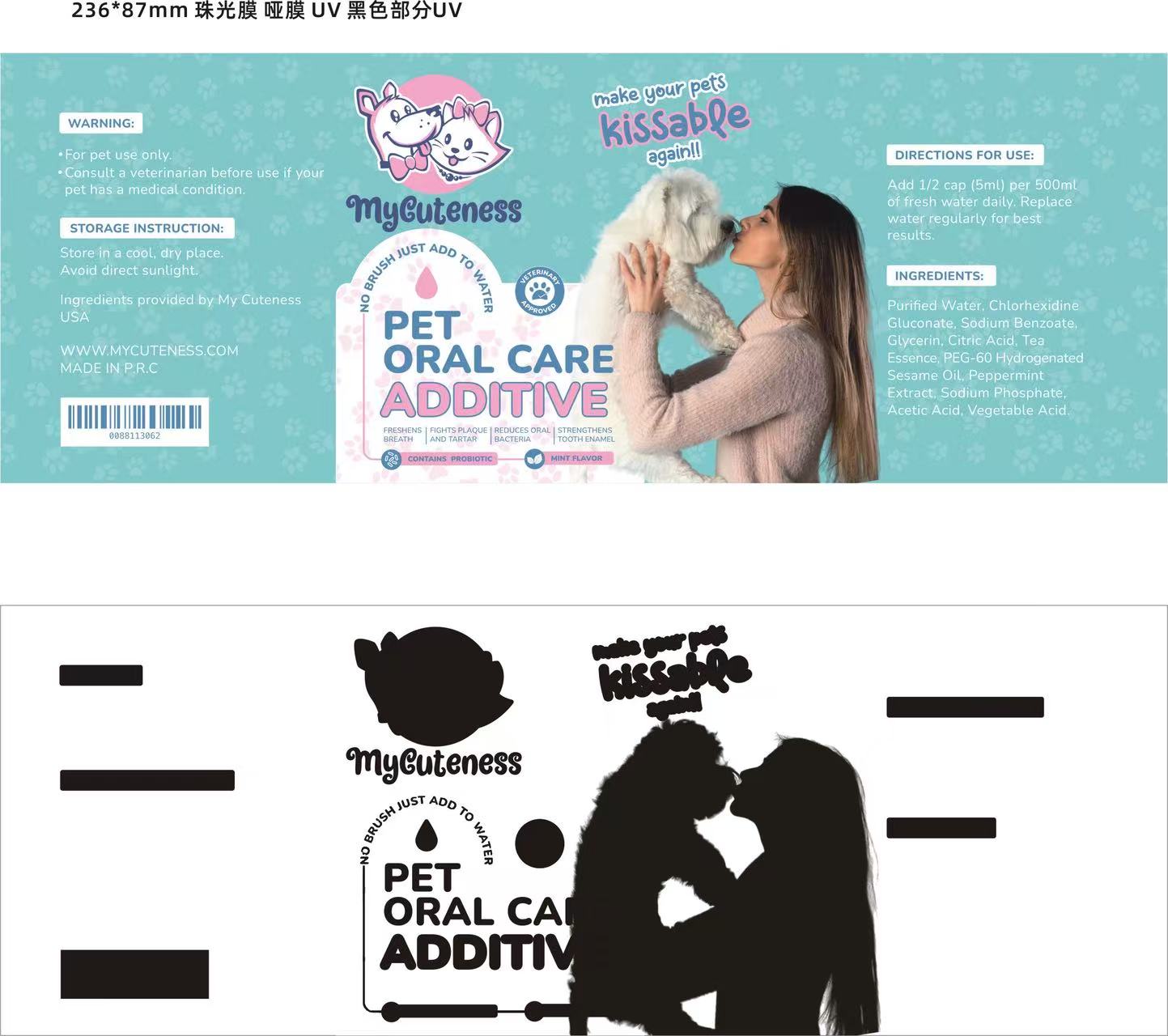 DRUG LABEL: MyCuteness Pet Dental Care Water Additive
NDC: 87154-003 | Form: LIQUID
Manufacturer: MY CUTENESS LLC
Category: animal | Type: OTC ANIMAL DRUG LABEL
Date: 20251007

ACTIVE INGREDIENTS: CHLORHEXIDINE DIGLUCONATE 0.08 g/100 mL
INACTIVE INGREDIENTS: CAMELLIA SINENSIS LEAF OIL; PHYTIC ACID; ACETIC ACID; WATER; GLYCERIN; PEPPERMINT; CITRIC ACID; PEG-60 HYDROGENATED CASTOR OIL; SODIUM BENZOATE; SODIUM PHOSPHATE

INGREDIENTS:

Purified Water, ChlorhexidineGluconate, Sodium BenzoateGlycerin, Citric Acid, TeaEssence, PEG-60 HydrogenatedSesame Oil. PeppermintExtract, Sodium Phosphate,Acetic Acid, Vegetable Acid

WARNING:

For pet use only.Consult a veterinarian before use if yourpet has a medical condition.

DOSAGE AND ADMINISTRATION

Add 1/2 cap (5ml) per 500m!of fresh water daily. Replacewater regularly for bestresults

INDICATIONS AND USAGE

Add 1/2 cap (5ml) per 500m!of fresh water daily. Replacewater regularly for bestresults

PET ORAL CARE ADDITIVE

WARNING:
For pet use only.Consult a veterinarian before use if yourpet has a medical condition.
STORAGE INSTRUCTION:Store in a cool, dry place.Avoid direct sunlight.
Ingredients provided by My CutenessUSA
WWW.MYCUTENESS.COMMADE IN PR.C
DIRECTIONS FOR USE:
Add 1/2 cap (5ml) per 500mlof fresh water daily. Replacewater regularly for bestresults.
INGREDIENTS:
Purified Water, ChlorhexidineGluconate, Sodium Benzoate,Glycerin, Citric Acid, TeaEssence, PEG-60 HydrogenatedSesame Oil. PeppermintExtract, Sodium Phosphate,Acetic Acid, Vegetable Acid
PET
ORAL CARE
ADDITIVE
FRESHENS |FIGHTS PLAQUE I REDUCES ORALSTRENGTHENSBREATHAND TARTARBACTERIATOOTH ENAMEL

Add image transcription here...